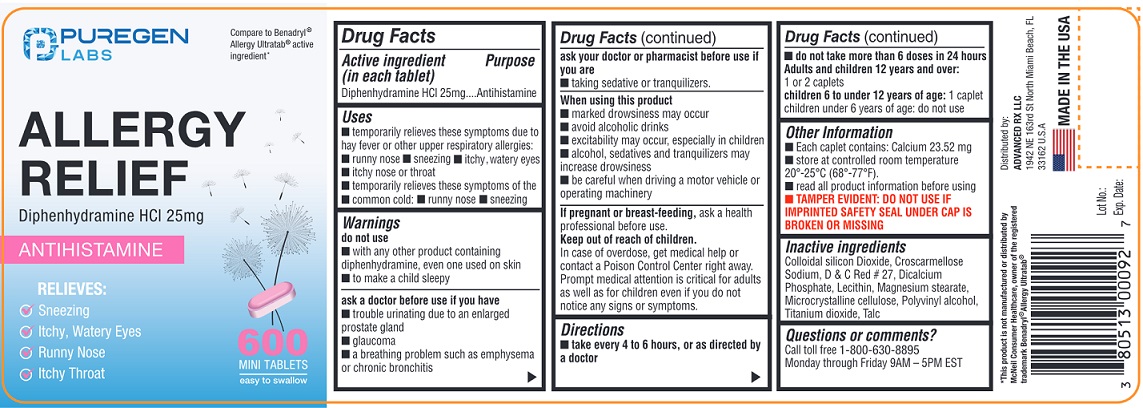 DRUG LABEL: Allergy Relief
NDC: 80513-722 | Form: TABLET
Manufacturer: Advanced Rx LLC
Category: otc | Type: HUMAN OTC DRUG LABEL
Date: 20250702

ACTIVE INGREDIENTS: DIPHENHYDRAMINE HYDROCHLORIDE 25 mg/1 1
INACTIVE INGREDIENTS: SILICON DIOXIDE; CROSCARMELLOSE SODIUM; D&C RED NO. 27; ANHYDROUS DIBASIC CALCIUM PHOSPHATE; MAGNESIUM STEARATE; MICROCRYSTALLINE CELLULOSE; POLYVINYL ALCOHOL, UNSPECIFIED; TITANIUM DIOXIDE; TALC

Active ingredient (in each tablet)

Diphenhydramine HCl 25 mg

Purpose

Antihistamine

Uses

- temporarily relieves these symptoms due to hay fever or other upper respiratory allergies:
  - runny nose
  - sneezing
  - itchy, watery eyes
  - itchy nose or throat
- temporarily relieves these symptoms of the common cold:
  - runny nose
  - sneezing

Warnings

do not use

- with any other product containing diphenhydramine, even one used on skin
- to make a child sleepy

ask a doctor before use if you have

- trouble urinating due to an enlarged prostate gland
- glaucoma
- a breathing problem such as emphysema or chronic bronchitis

ask your doctor or pharmacist before use if you are

- taking sedatives or tranquilizers.

When using this product

- marked drowsiness may occur
- avoid alcoholic beverages
- excitability may occur, especially in children
- alcohol, sedatives, and tranquilizers may increase drowsiness
- be careful when driving a motor vehicle or operating machinery

PREGNANCY OR BREAST FEEDING

If pregnant or breast-feeding,ask a health professional before use.

Keep out of reach of children.

In case of overdose, get medical help or contact a Poison Control Center right away.

Prompt medical attention is critical for adults as well as for children even if you do not notice any signs or symptoms.

Directions

- take every 4 to 6 hours, or as directed by a doctor
- do not take more than 6 doses in 24 hours

Adults and children 12 years and over:1 or 2 caplets

Children 6 to under 12 years of age:1 caplet

Children under 6 years of age: do not use

Other information

- Each caplet contains:Calcium 23.52 mg
- store at controlled room temperature 20°-25°C (68°-77°F)
- read all product information before using.
- TAMPER EVIDENT: DO NOT USE IF IMPRINTED SAFETY SEAL UNDER CAP IS BROKEN OR MISSING.

Inactive ingredients

Colloidal Silicon Dioxide, Croscarmellose Sodium, D&C Red #27, Dicalcium Phosphate, Lecithin, Magnesium Stearate, Microcrystalline Cellulose, Polyvinyl alcohol, Titanium dioxide, Talc

Questions or comments?

Call toll free 1-800-630-8895

Monday through Friday 9 AM - 5 PM EST.

Distributed by:

Advanced Rx LLC

1942 NE 163rd St North Miami Beach,

FL 33162 U.S.A.

MADE IN THE USA

PACKAGE LABEL

NDC 80513-722-06

Compare to Benadryl®Allergy Ultratab®active ingredient*

ALLERGY RELIEF

DIPHENHYDRAMINE HCl 25 mg

ANTIHISTAMINE

RELIEVES:

Sneezing

Itchy, Watery Eyes

Runny Nose
Itchy Throat

600

MINI TABLETS

*This product is not manufactured or distributed by McNeil-Consumer Healthcare, owner of the registered trademark Benadryl®Allergy Ultratab®